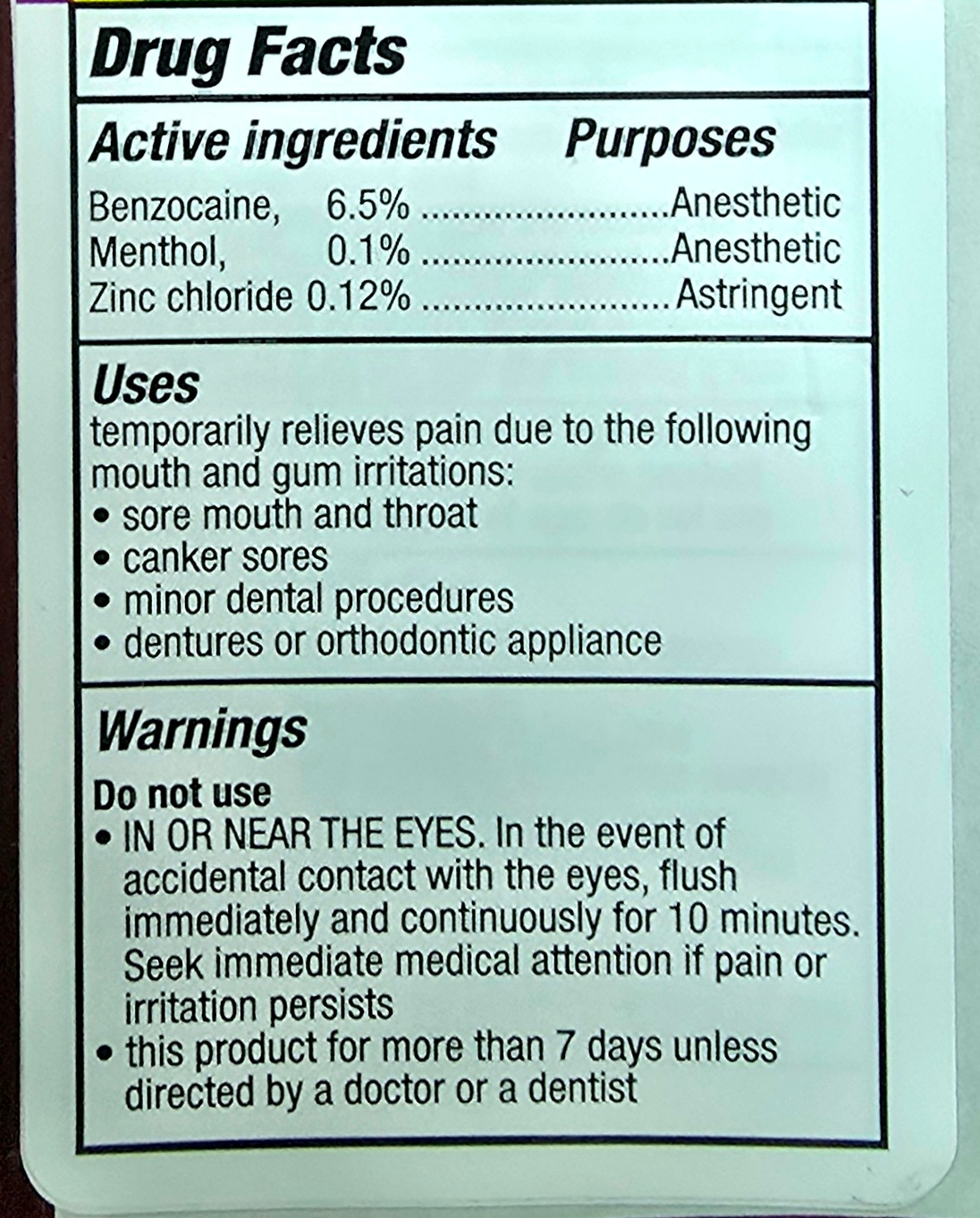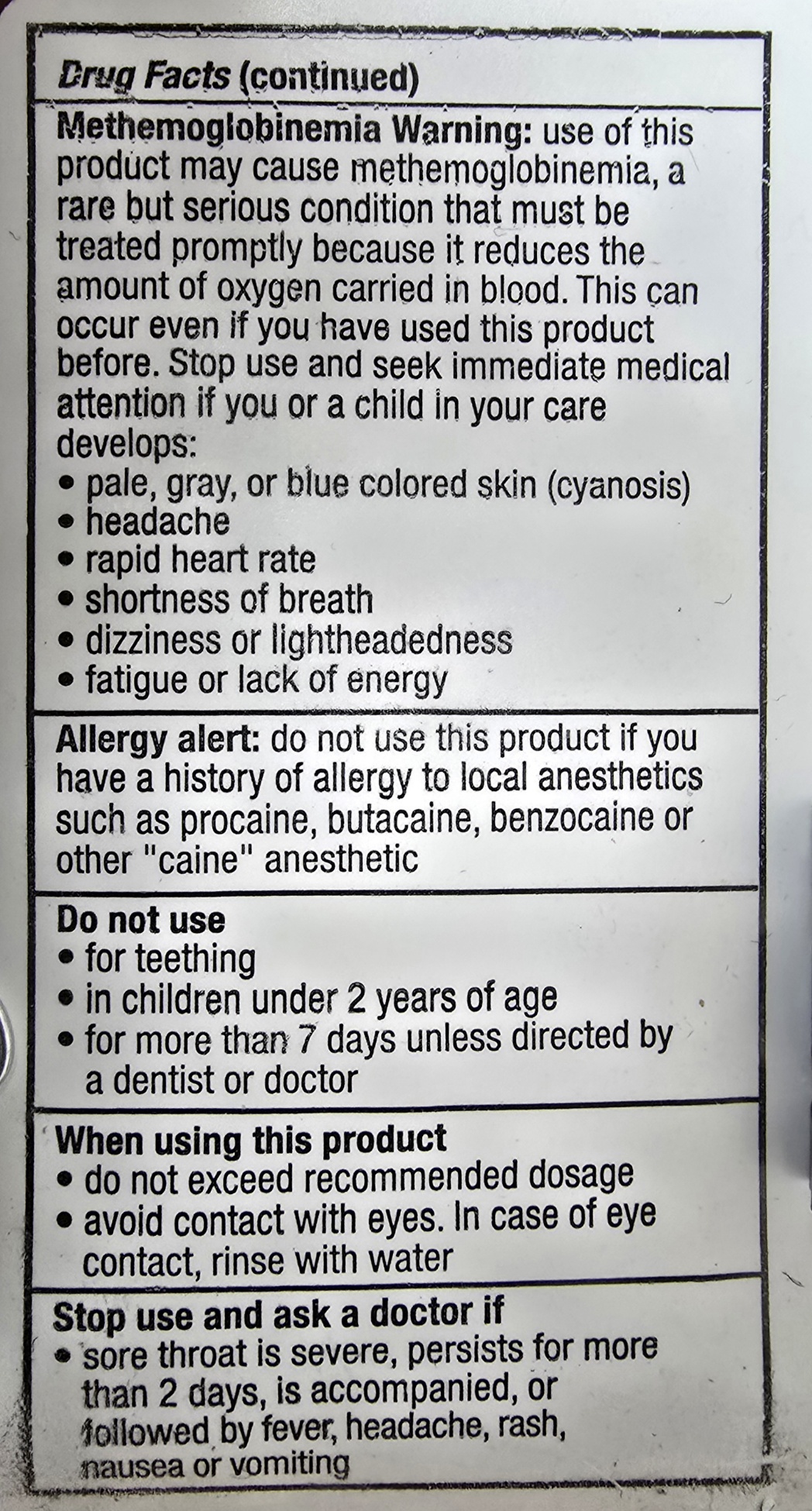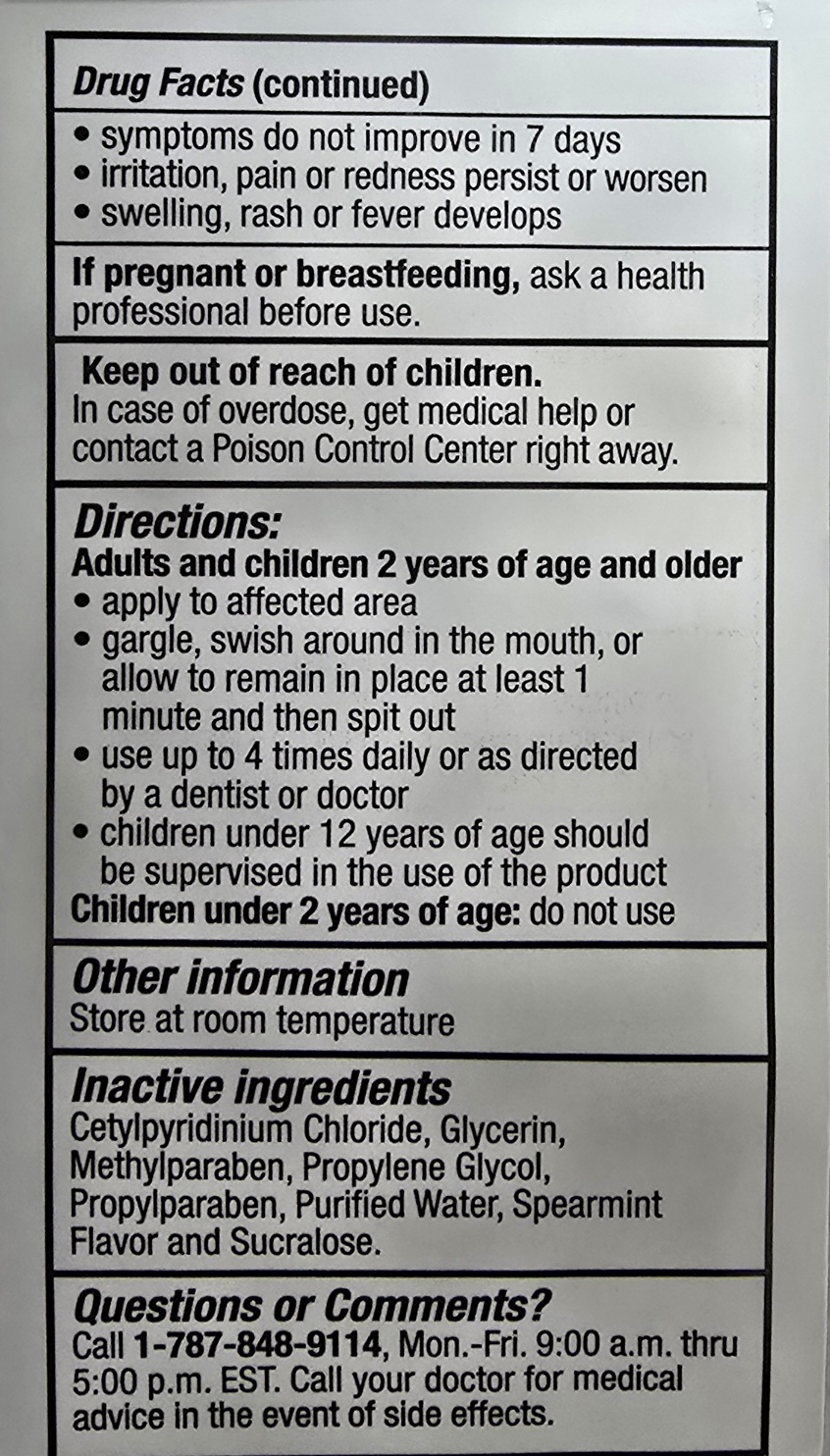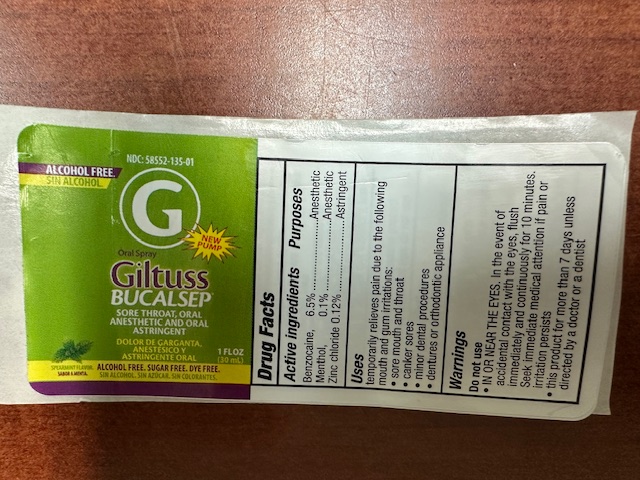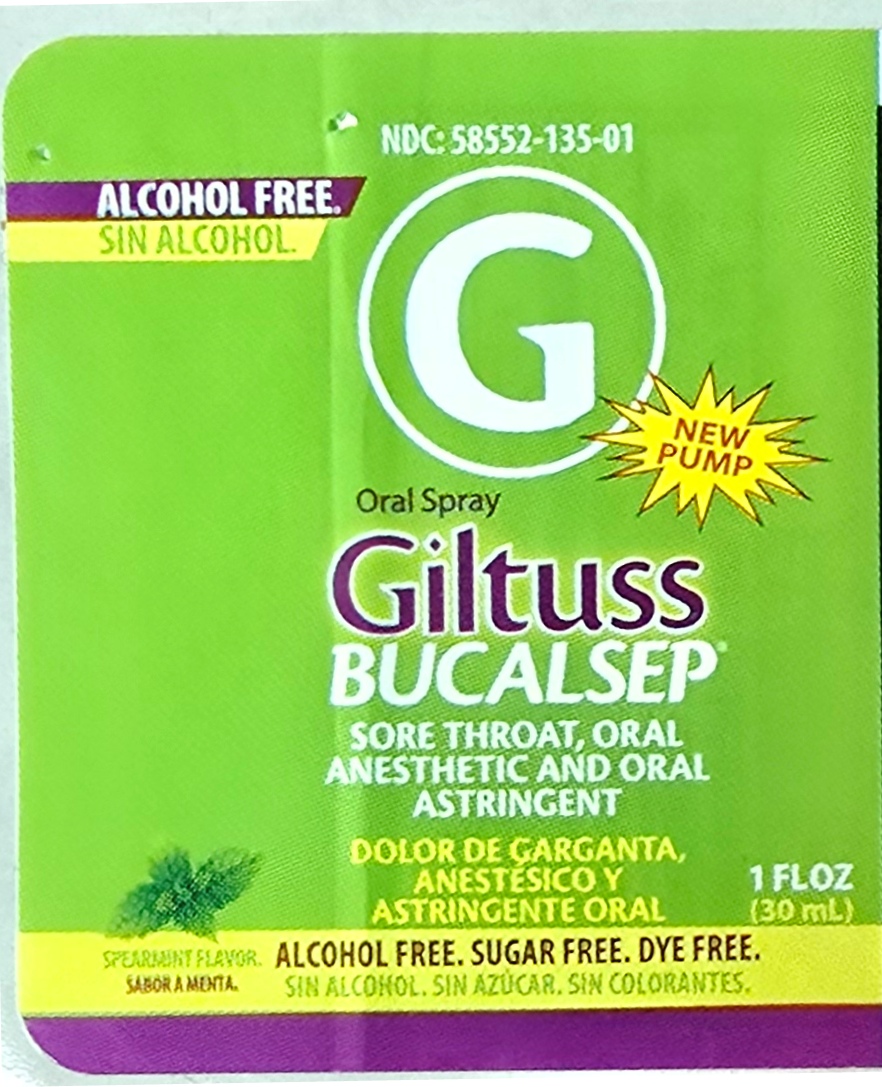 DRUG LABEL: Giltuss Bucalsep
NDC: 65852-015 | Form: SPRAY
Manufacturer: Dextrum Laboratories Inc.
Category: otc | Type: HUMAN OTC DRUG LABEL
Date: 20250925

ACTIVE INGREDIENTS: ZINC CATION 0.12 mg/100 mL; BENZOCAINE 6.5 mg/100 mL; MENTHOL 0.1 mg/100 mL
INACTIVE INGREDIENTS: PROPYLPARABEN; CETYLPYRIDINIUM CHLORIDE; GLYCERIN; METHYLPARABEN; WATER; PROPYLENE GLYCOL; SUCRALOSE

Giltuss Bucalsep

Active Ingredients

Active ingredients Purpose

Benzocaine, 6.5% ----------------- Anesthesic

Menthol, 0.1% ----------------------- Anesthesic

Zinc Chloride 0.12% --------------- Astringent

Uses

temporary relieves pain due to the following mouth and gum irritations

- sore mouth and throat
- canker sores
- minor dental procedures
- dentures or orthodontic appliance

Warnings

Do not use

- IN OR NEAR THE EYES. In the event of accidental contact with the eyes, flush immediately and continuosly for 10 minutes. Seek immediate medical attention if pain or irritations persists.
- this product for more than 7 days unless directed by a doctor or a dentist

Methemoglobinemia Warning: use of this product may cause methemoglobinemia, a rare but serious condition that must be treated promptly because it reduces the amount of oxygen carried in blood. This can occur even if you have used this product before.Stopo use and seek immediate medical attention if you or a child in your care develops:

- pale, gray or blue colored skin (cyanosis)
- headache
- rapid heart rate
- shortness of breath
- dizziness or lightheadedness
- fatigue or lack of energy

Allergy alert: do not use this product if you have a history of allergy to local anesthetics such as procaine, butacaine, benzocaine or other "caine" anesthetic

Do not use

- for teething
- in children under 2 years of age
- for more than 7 days unless directed by a dentist or doctor

When using this product

- do not exceed recommended dosage
- avoid contact with eyes. In case of eye contact, rinse with water

Stop use and ask a doctor if

- Sore throat is severe, persist for more than 2 days, is accompanied, or followed by fever, headache, rash,nausea or vomiting
- Symptoms do not improve in 7 days
- irritation, pain or redness persist or worsen
- swelling, rash or fever develops

If pregnant or breastfeeding, ask a health professional before use

Keep out of reach of children

In case of overdose, get medical help or contact a Poison Control Center right away

Directions

Adults and children 2 years of age and older

- apply to affected area
- gargle, swish around in the mouth, or allow to remain in place at least 1 minute and then spit out
- use 4 times daily or as directed by dentist or doctor
- children under 12 years of age should be supervised in the use of the product

Children under 2 years of age: do not use

Other information

Store at room temperature

Inactive Ingredients

Cetylpyridinium chloride, glycerin, Methylparaben, Proylene Glycol, Propylparaben, Purified Water, Spearmint Flavor and Sucralose.

Questions or comments?

Questions or comments?

Call 1-787-848-9114, Monday-Friday 9AM – 5PM EST

Call your doctor for medical advice in the event of side effects.

Indication and usage section

Adults and children 2 years of age and older

apply to affected area
gargle, swish around in the mouth, or allow to remain in place at least 1 minute and then spit out
use 4 times daily or as directed by dentist or doctor
children under 12 years of age should be supervised in the use of the product

Children under 2 years of age: do not use

PACKAGE LABEL

NDC: 58552-135-01

Alcohol free

Oral Spray

Giltuss Bucalsep

Sore, Throat, Oral astringent

1 floz (30 mL)

Alcohol free, sugar free, dye free

Spearmint flavor